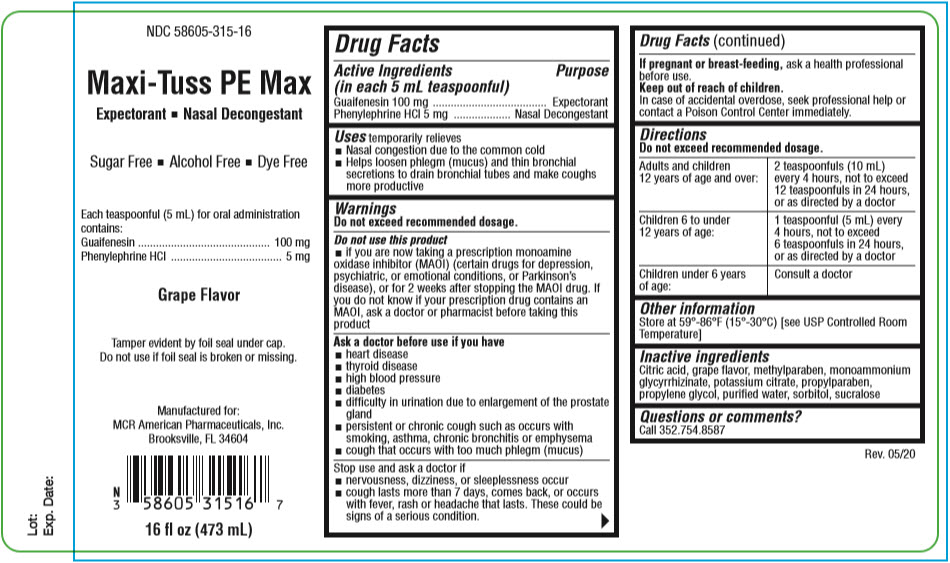 DRUG LABEL: Maxi-Tuss PE Max
NDC: 58605-315 | Form: LIQUID
Manufacturer: MCR American Pharmaceuticals, Inc.
Category: otc | Type: HUMAN OTC DRUG LABEL
Date: 20200625

ACTIVE INGREDIENTS: GUAIFENESIN 100 mg/5 mL; Phenylephrine Hydrochloride 5 mg/5 mL
INACTIVE INGREDIENTS: CITRIC ACID MONOHYDRATE; Methylparaben; AMMONIUM GLYCYRRHIZATE; Potassium Citrate; Propylparaben; Propylene Glycol; WATER; Sorbitol; Sucralose

Maxi-Tuss PE Max

Drug Facts

ACTIVE INGREDIENT

Active Ingredients (in each 5 mL teaspoonful) | Purpose
Guaifenesin 100 mg | Expectorant
Phenylephrine HCl 5 mg | Nasal Decongestant

Uses

temporarily relieves

- Nasal congestion due to the common cold
- Helps loosen phlegm (mucus) and thin bronchial secretions to drain bronchial tubes and make coughs more productive

Warnings

Do not exceed recommended dosage.

Do not use this product

- if you are now taking a prescription monoamine oxidase inhibitor (MAOI) (certain drugs for depression, psychiatric, or emotional conditions, or Parkinson's disease), or for 2 weeks after stopping the MAOI drug. If you do not know if your prescription drug contains an MAOI, ask a doctor or pharmacist before taking this product

Ask a doctor before use if you have

- heart disease
- thyroid disease
- high blood pressure
- diabetes
- difficulty in urination due to enlargement of the prostate gland
- persistent or chronic cough such as occurs with smoking, asthma, chronic bronchitis or emphysema
- cough that occurs with too much phlegm (mucus)

Stop use and ask a doctor if

- nervousness, dizziness, or sleeplessness occur
- cough lasts more than 7 days, comes back, or occurs with fever, rash or headache that lasts. These could be signs of a serious condition.

PREGNANCY OR BREAST FEEDING

If pregnant or breast-feeding, ask a health professional before use.

Keep out of reach of children.

In case of accidental overdose, seek professional help or contact a Poison Control Center immediately.

Directions

Do not exceed recommended dosage.

Adults and children 12 years of age and over: | 2 teaspoonfuls (10 mL) every 4 hours, not to exceed 12 teaspoonfuls in 24 hours, or as directed by a doctor
Children 6 to under 12 years of age: | 1 teaspoonful (5 mL) every 4 hours, not to exceed 6 teaspoonfuls in 24 hours, or as directed by a doctor
Children under 6 years of age: | Consult a doctor

Other information

Store at 59°-86°F (15°-30°C) [see USP Controlled Room Temperature]

Inactive ingredients

Citric acid, grape flavor, methylparaben, monoammonium glycyrrhizinate, potassium citrate, propylparaben, propylene glycol, purified water, sorbitol, sucralose

Questions or comments?

Call 352.754.8587

PRINCIPAL DISPLAY PANEL - 473 mL Bottle Label

NDC 58605-315-16

Maxi-Tuss PE Max

Expectorant ◾ Nasal Decongestant

Sugar Free ◾ Alcohol Free ◾ Dye Free

Each teaspoonful (5 mL) for oral administration
contains:
Guaifenesin 100 mg
Phenylephrine HCl 5 mg

Grape Flavor

Tamper evident by foil seal under cap.
Do not use if foil seal is broken or missing.

Manufactured for:
MCR American Pharmaceuticals, Inc.
Brooksville, FL 34604

16 fl oz (473 mL)